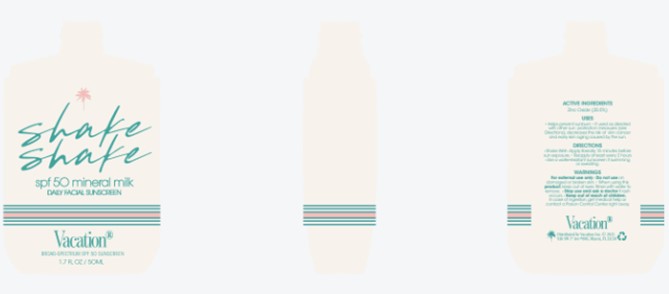 DRUG LABEL: Mineral Shake
NDC: 80641-014 | Form: LOTION
Manufacturer: Vacation Inc.
Category: otc | Type: HUMAN OTC DRUG LABEL
Date: 20240313

ACTIVE INGREDIENTS: ZINC OXIDE 20.5 g/100 mL
INACTIVE INGREDIENTS: BUTYLOCTYL SALICYLATE

Vacation SPF 50 Mineral Shake

Dosage and administration

Apply liberally 15 minutes before sun exposure

Reapply at least every 2 hours

Use a water resistant sunscreen if swimming or sweating

Warnings

For external use only

Do not use on damaged or broken skin

When using this product, keep out of eyes. Rinsed with water to remove.

Stop use and ask a doctor is rash occurs

Indications and Usage

Helps prevent sunburn

If used as directed with other sun protection measures (see Directions), decreases the risk of skin cancer and early skin aging caused by the sun

Keep out of reach of children

Purpose

Sunscreen

Inactives

Aloe Barbadensis Leaf Juice, Butyloctyl Salicylate, Butyrospermum Parkii (Shea) Oil, C12-15 Alkyl Benzoate, Camellia Sinensis Leaf Extract, Caprylhydroxamic Acid, Caprylic/Capric Triglyceride, Carbomer, Ceramide AP, Ceramide EOP, Ceramide NP

Cholesterol, Cucumis Sativus (Cucumber) Fruit Extract, Dihydro Myrcenol, Diisostearoyl Polyglyceryl-3 Dimer Dilinoleate, Dimethicone, Ethylhexyl Methoxycrylene, Ethylhexyl Olivate, Ethylhexylglycerin, Ferulic Acid, Floralozone, Glycerin, Gossypium Herbaceum (Cotton) Seed Oil, Hexyl Cinnamic Aldehyde, Hyaluronic Acid, Isododecane, Magnesium Sulfate, Methyl Octyne Carbonate, Niacinamide, Passiflora Edulis Seed Oil, Phenoxyethanol, Phytosphingosine, Polyglyceryl-3 Oleate

Polyglyceryl-4 Diisostearate/Polyhydroxystearate/Sebacate, Polyglyceryl-4 Isostearate, Polyhydroxystearic Acid, Scentenal, Sodium Benzoate, Sodium Gluconate, Sodium Lauroyl Lactylate, Squalane, sr-Hydrozoan Polypeptide-1, Tocopherol, Triethoxycaprylylsilane

Undecavertol, Water, Xanthan Gum